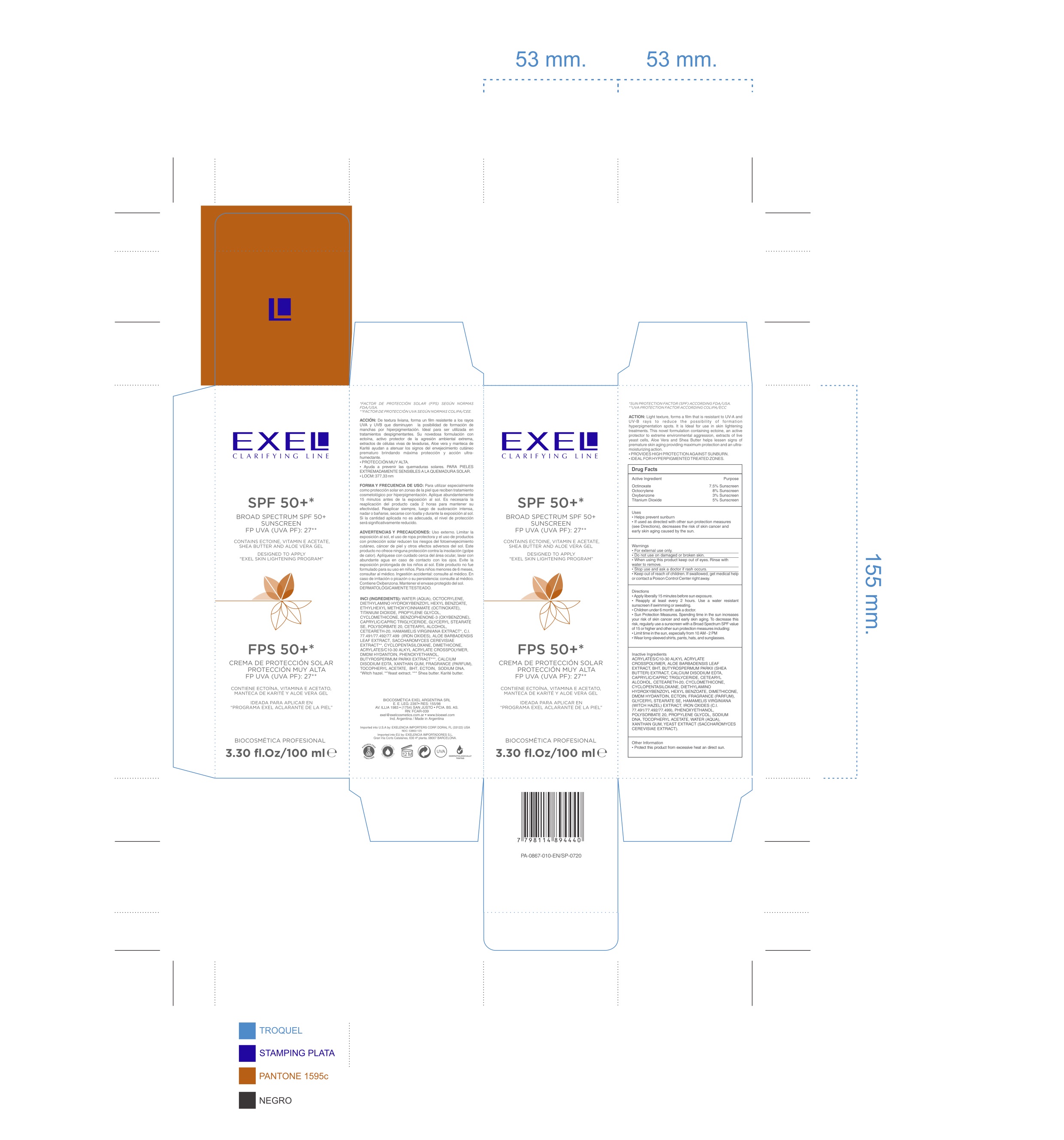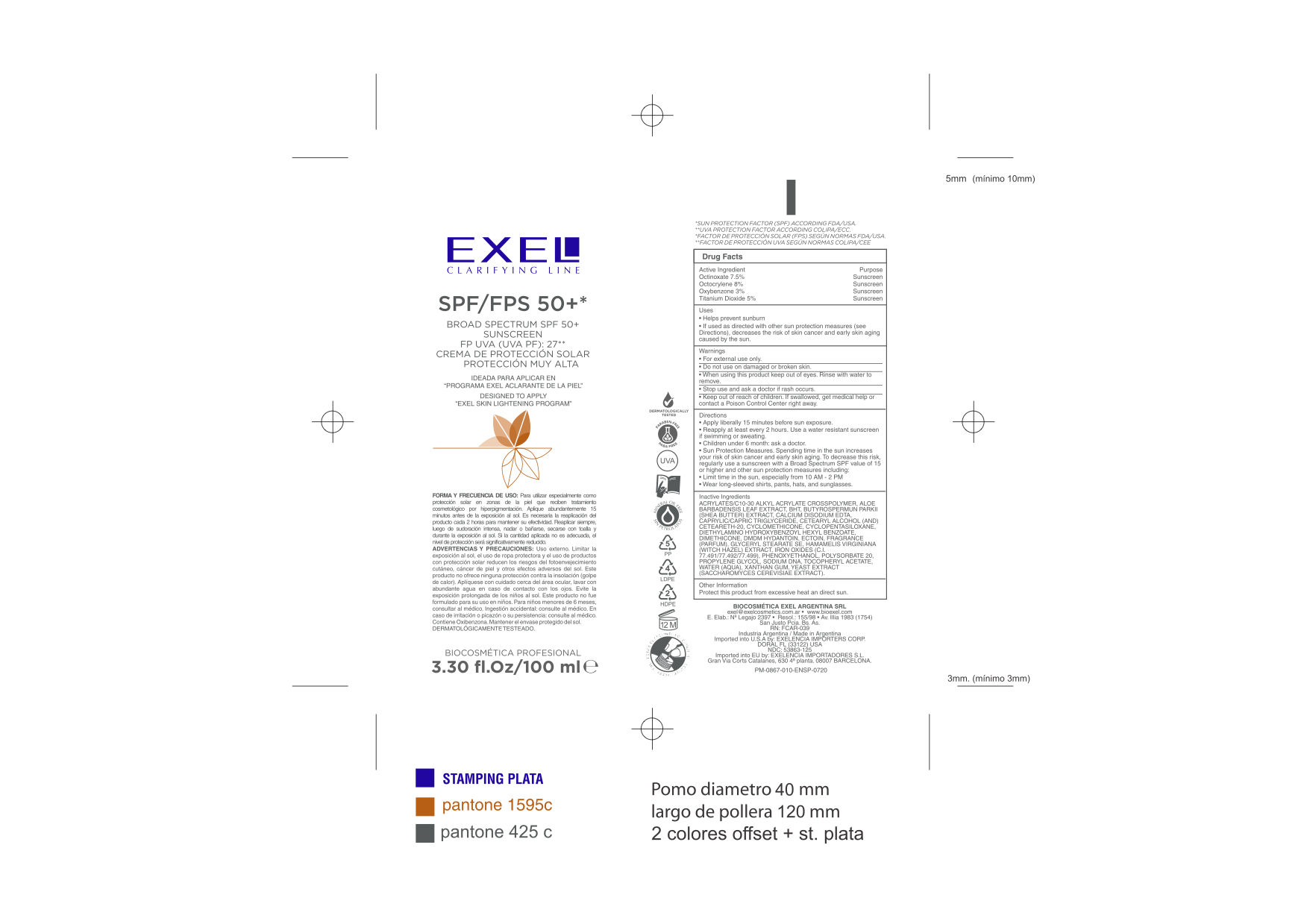 DRUG LABEL: Exel Clarifying Line
NDC: 53863-125 | Form: CREAM
Manufacturer: Exelencia importers
Category: otc | Type: HUMAN OTC DRUG LABEL
Date: 20240630

ACTIVE INGREDIENTS: OCTINOXATE 7.5 g/100 mL; OCTOCRYLENE 8 g/100 mL; OXYBENZONE 3 g/100 mL; TITANIUM DIOXIDE 5 g/100 mL
INACTIVE INGREDIENTS: CARBOMER INTERPOLYMER TYPE A (ALLYL SUCROSE CROSSLINKED); ALOE VERA LEAF; BUTYLATED HYDROXYTOLUENE; SHEANUT OIL; EDETATE CALCIUM DISODIUM ANHYDROUS; MEDIUM-CHAIN TRIGLYCERIDES; CETOSTEARYL ALCOHOL; POLYOXYL 20 CETOSTEARYL ETHER; CYCLOMETHICONE; CYCLOMETHICONE 5; DIETHYLAMINO HYDROXYBENZOYL HEXYL BENZOATE; DIMETHICONE; DMDM HYDANTOIN; ECTOINE; GLYCERYL STEARATE SE; HAMAMELIS VIRGINIANA TOP; FERRIC OXIDE RED; FERRIC OXIDE YELLOW; FERROSOFERRIC OXIDE; PHENOXYETHANOL; POLYSORBATE 20; PROPYLENE GLYCOL; .ALPHA.-TOCOPHEROL ACETATE; WATER; XANTHAN GUM; YEAST, UNSPECIFIED

Exel Clarifying Line SPF 50

Active Ingredient ........ Purpose

Octinoxate 7.5% ........ Sunscreen
Octocrylene 8% ........ Sunscreen

Oxybenzone 3% ........ Sunscreen

Titanium Dioxide 5% ........ Sunscreen

Uses

- Helps prevent sunburn

- If used as directed with other sun protection measures (See directions), decreases the risk of skin cancer and early skin aging caused by the sun

Keep out of reach of children. If swallowed, get medical help or contact a Poison Control Center right away.

Stop use and ask a doctor if rash occurs

Directions

- Apply liberally 15 minutes before sun exposure

- Reapply at least every 2 hours

- Children under 6 month: ask a doctor

-Sun protection measures. Spending time in the sun increases your risk of skin cancer and early skin aging. To decrease this risk, regularly use a sunscreen with a Broad Spectrum SPF value of 15 or higher and other sun protection measures including:

Limit time in the sun, Especially from 10 AM - 2 PMWear long-sleeved shirts, pants, hats, and sunglassesUse a water resistant sunscreen if swimming or sweating

INACTIVE INGREDIENT

Acrylates/C10-30 Alkyl Acrylate Crosspolymer, Aloe Barbadensis Leaf Extract, BHT, Butyrospermum Parkii (shea butter) Extract, Calcium Disodium EDTA, Caprylic/Capric Triglyceride, Cetearyl Alcohol (and) Ceteareth-20, Cyclomethicone, Cyclopentasiloxane, Diethlyamino Hydroxybenzoyl Hexyl Benzoate, Dimethicone, DMDM Hydantoin, Ectoin, Fragrance (Parfum), Glyceryl Stearate SE, Hamamelis Virginiana (witch hazel) Extract, Iron Oxides (C.I. 77497/77492/77499), Phenoxyethanol, Polysorbate 20, Propylene Glycol, Sodium DNA, Tocopheryl Acetate, Water (Aqua), Xanthan Gum, Yeast Extract (saccharomyces cerevisiae extract)

WARNINGS

For external use only.

Do not use on damaged or broken skin.

When using this product keep out of eyes. Rinse with water to remove.

Stop use and ask a doctor if rash occurs.

Keep out of children. If swallowed get medical help or contact a Poison Control Center right away.

PACKAGE LABEL

Exel Clarifying Line

SPF 50

Broad Spectrum SPF 50

3.30 fl.oz / 100 ml